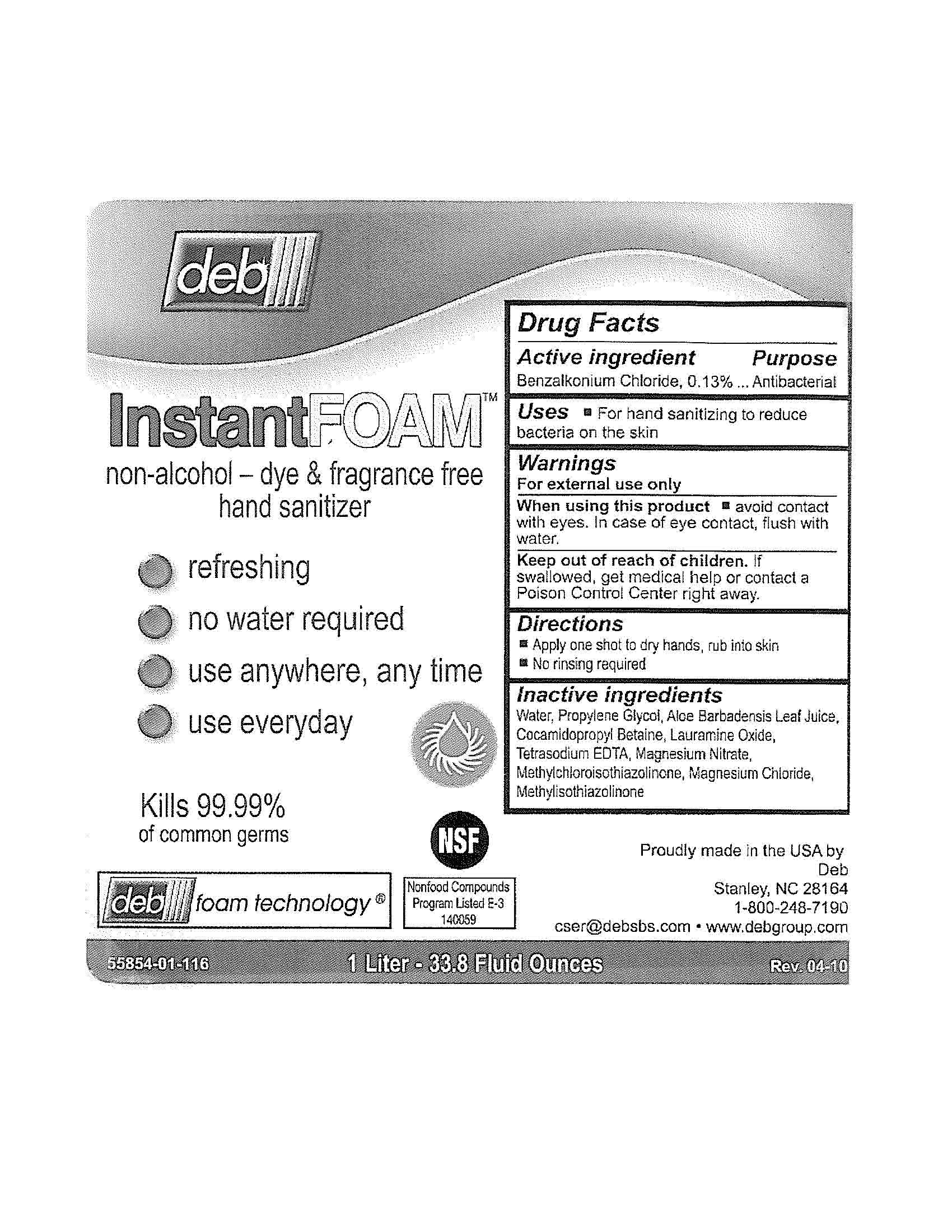 DRUG LABEL: InstantFOAM non-alcohol
NDC: 11084-058 | Form: LIQUID
Manufacturer: Deb USA, Inc.
Category: otc | Type: HUMAN OTC DRUG LABEL
Date: 20100930

ACTIVE INGREDIENTS: BENZALKONIUM CHLORIDE 0.13 mL/100 mL
INACTIVE INGREDIENTS: WATER; PROPYLENE GLYCOL; ALOE VERA LEAF; COCAMIDOPROPYL BETAINE; LAURAMINE OXIDE; EDETATE SODIUM; METHYLCHLOROISOTHIAZOLINONE; METHYLISOTHIAZOLINONE; MAGNESIUM NITRATE; MAGNESIUM CHLORIDE

Drug Facts

Active ingredient

Benzalkonium Chloride, 0.13%

Purpose

Antibacterial

Uses

For hand sanitizing to reduce bacteria on the skin

Warnings

For external use only

When using this product avoid contact with eyes.

In case of eye contact, flush with water.

Keep out of reach of children.

If swallowed, get medical help or contact a Poison Control Center right away.

Directions

Apply one shot to dry hands, rub into skin

No rinsing required

Inactive ingredients

Water, Propylene Glycol, Aloe Barbadensis Leaf Juice, Cocamidopropyl Betaine, Lauramine Oxide, Tetrasodium EDTA, Magnesium Nitrate, Methylchloroisothiazolinone, Mangnesium Chloride, Methylisothiazolinone

PACKAGE LABEL

deb

InstantFOAM

non-alcohol-dye and fragrance free

hand sanitizer

refreshing

no water required

use anywhere, anytime

use everyday

Kills 99.99% of common germs

deb foam technology

NSF

Nonfood Compounds Program Listed E-3 140059

55854-01-116

1 Liter - 33.8 Fluid Ounces